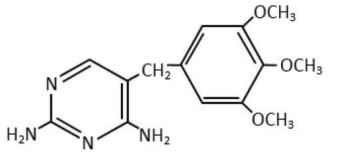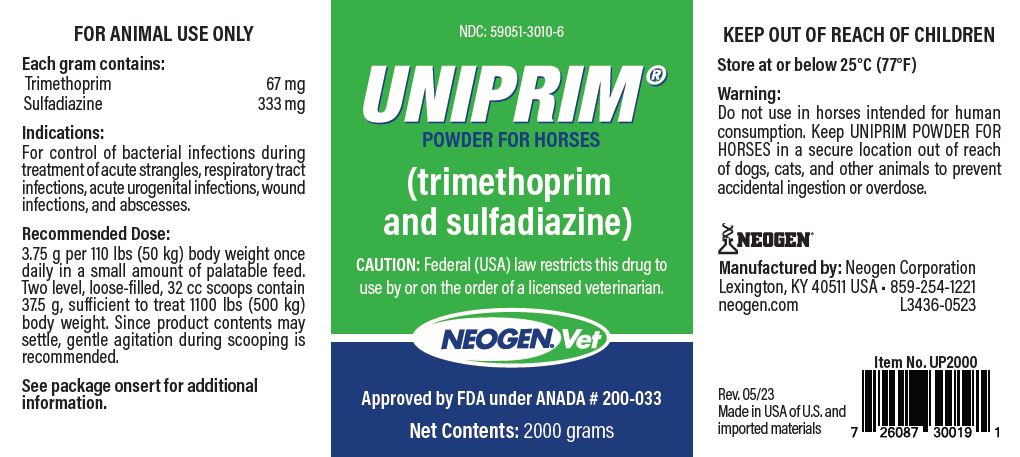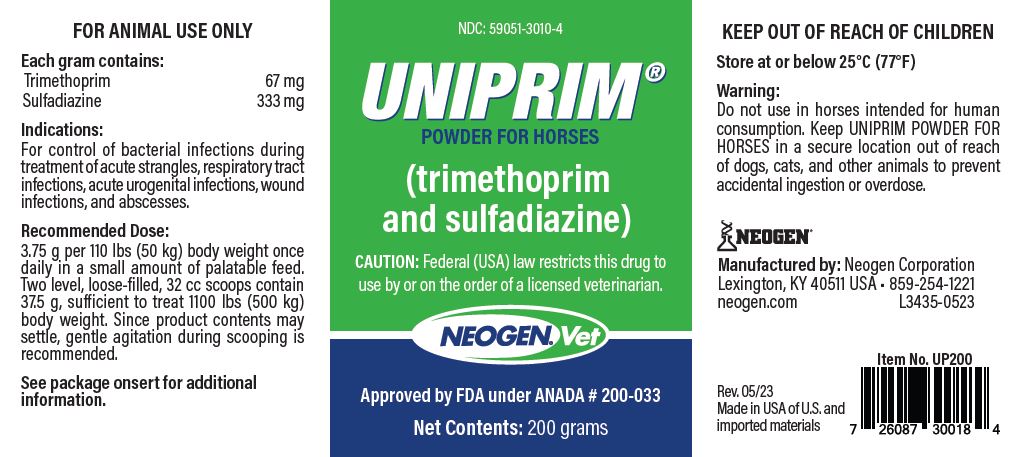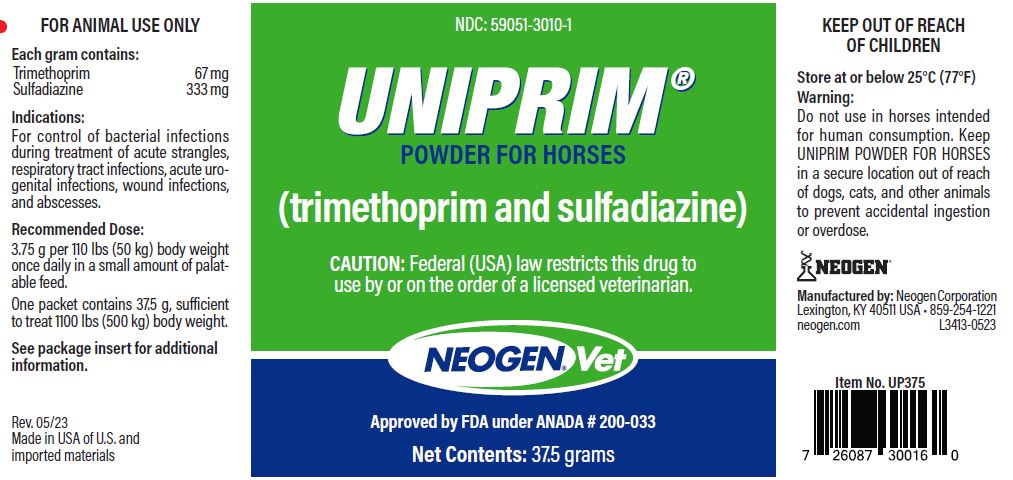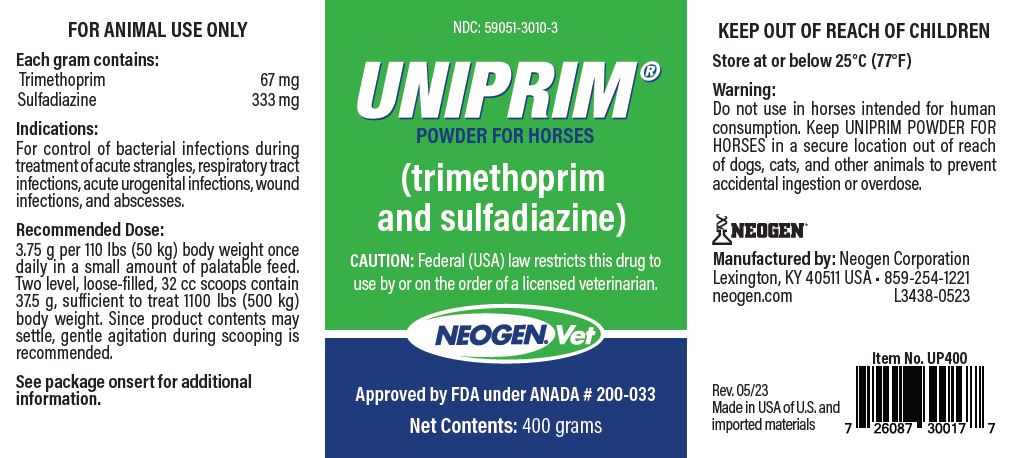 DRUG LABEL: UNIPRIM
NDC: 59051-3010 | Form: POWDER
Manufacturer: Neogen Corporation
Category: animal | Type: PRESCRIPTION ANIMAL DRUG LABEL
Date: 20231221

ACTIVE INGREDIENTS: Trimethoprim 67 mg/1 g; Sulfadiazine 333 mg/1 g

UNIPRIM POWDER FOR HORSES

DESCRIPTION

UNIPRIM POWDER FOR HORSES contains 67 mg trimethoprim and 333 mg sulfadiazine per gram.

UNIPRIM POWDER FOR HORSES is a combination of trimethoprim and sulfadiazine in the ratio of 1 part to 5 parts by weight, which provides effective antibacterial activity against a wide range of bacterial infections in animals.

Trimethoprim is 2, 4 diamino-5-(3,4,5-trimethoxybenzyl) pyrimidine.

ACTIONS

Microbiology: Trimethoprim blocks bacterial production of tetrahydrofolic acid from dihydrofolic acid by binding to and reversibly inhibiting the enzyme dihydrofolate reductase.

Sulfadiazine, in common with other sulfonamides, inhibits bacterial synthesis of dihydrofolic acid by competing with para-aminobenzoic acid.

Trimethoprim and sulfadiazine thus imposes a sequential double blockade on bacterial metabolism. This deprives bacteria of nucleic acids and proteins essential for survival and multiplication, and produces a high level of antibacterial activity which is usually bactericidal.

Although both sulfadiazine and trimethoprim are antifolate, neither affects the folate metabolism of animals. The reasons are: animals do not synthesize folic acid and cannot, therefore, be directly affected by sulfadiazine; and although animals must reduce their dietary folic acid to tetrahydrofolic acid, trimethoprim does not affect this reduction because its affinity for dihydrofolate reductase of mammals is significantly less than for the corresponding bacterial enzyme.

Trimethoprim and sulfadiazine is active against a wide spectrum of bacterial pathogens, both gram-negative and gram-positive. The following in vitro data are available, but their clinical significance is unknown. In general, species of the following genera are sensitive to trimethoprim and sulfadiazine:

Very Sensitive | Sensitive | Moderately Sensitive | Not Sensitive
Escherichia | Staphylococcus | Moraxella | Mycobacterium
Streptococcus | Neisseria | Nocardia | Leptospira
Proteus | Klebsiella | Brucella | Pseudomonas
Salmonella | Fusiformis |  | Erysipelothrix
Pasteurella | Corynebacterium
Shigella | Clostridium
Haemophilus | Bordetella

As a result of the sequential double blockade of the metabolism of susceptible organisms by trimethoprim and sulfadiazine, the minimum inhibitory concentration (MIC) of trimethoprim and sulfadiazine is markedly less than that of either of the components used separately. Many strains of bacteria that are not susceptible to one of the components are susceptible to trimethoprim and sulfadiazine. A synergistic effect between trimethoprim and sulfadiazine in combination has been shown experimentally both in vitro and in vivo (in dogs).

Trimethoprim and sulfadiazine is bactericidal against susceptible strains and is often effective against sulfonamide-resistant organisms. In vitro sulfadiazine is usually only bacteriostatic.

The precise in vitro MIC of the combination varies with the ratio of the drugs present, but action of trimethoprim and sulfadiazine occurs over a wide range of ratios with an increase in the concentration of one of its components compensating for a decrease in the other. It is usual, however, to determine MICs using a constant ratio of 1 part trimethoprim in 20 parts of the combination.

The following table shows MICs, using the above ratio, of bacteria which were susceptible to both trimethoprim (TMP) and sulfadiazine (SDZ). The organisms are those most commonly involved in conditions for which trimethoprim and sulfadiazine is indicated:

AVERAGE MINIMUM INHIBITORY CONCENTRATION (MIC-mcg/mL)
Bacteria | TMP; Alone | SDZ; Alone | TMP/SDZ
Bacteria | TMP; Alone | SDZ; Alone | TMP | SDZ
Escherichia coli Proteus species Staphylococcus aureus Pasteurella species Salmonella species ß Streptococcus | 0.31; 1.30; 0.60; 0.06; 0.15; 0.5 | 26.5; 24.5; 17.6; 20.1; 61.0; 24.5 | 0.07; 0.15; 0.13; 0.03; 0.05; 0.15 | 1.31; 2.85; 2.47; 0.56; 0.95; 2.85

The following table demonstrates the marked effect of the trimethoprim and sulfadiazine combination against sulfadiazine-resistant strains of normally susceptible organisms:

AVERAGE MINIMUM INHIBITORY CONCENTRATION OF SULFADIAZINE-RESISTANT STRAINS (MIC-mcg/mL)
Bacteria | TMP; Alone | SDZ; Alone | TMP/SDZ
Bacteria | TMP; Alone | SDZ; Alone | TMP | SDZ
Escherichia coli Proteus species | 0.32; 0.66 | >245; >245 | 0.27; 0.32 | 5.0; 6.2

Susceptibility Testing: In testing susceptibility to trimethoprim and sulfadiazine, it is essential that the medium used does not contain significant amounts of interfering substances which can bypass the metabolic blocking action, e.g., thymidine or thymine.

The standard SxT disc is appropriate for testing by the disc diffusion method.

Pharmacology: Following oral administration, trimethoprim and sulfadiazine is rapidly absorbed and widely distributed throughout body tissues. Concentrations of trimethoprim are usually higher in tissues than in blood. The levels of trimethoprim are high in lungs, kidney, and liver, as would be expected from its physical properties.

Serum trimethoprim concentrations in horses following oral administration indicate rapid absorption of the drug; peak concentrations occur in 1.5 hours. The mean serum elimination half-life is 2 to 2.5 hours. Sulfadiazine absorption is slower, requiring 2.5 to 6 hours to reach peak concentrations. The mean serum elimination half-life for sulfadiazine is about 4 to 5.5 hours.

Usually, the concentration of an antibacterial in the blood and the in vitro MIC of the infecting organism indicate an appropriate period between doses of a drug. This does not hold entirely for trimethoprim and sulfadiazine because trimethoprim, in contrast to sulfadiazine, localizes in tissues and therefore its concentration and ratio to sulfadiazine are higher there than in blood.

The following table shows the average concentration of trimethoprim and sulfadiazine, as measured in either serum or plasma, in twenty-four adult horses observed after a single dose of UNIPRIM POWDER FOR HORSES:

AVERAGE SERUM/PLASMA CONCENTRATION (mcg/mL)
Trimethoprim (5 mg/kg) |  |  |  |  | Sulfadiazine (25 mg/kg)
1 hr; 0.82 | 3 hr; 0.69 | 6 hr; 0.36 | 10 hr; 0.12 | 24 hr; <0.025 | 1 hr; 9.9 | 3 hr; 18.8 | 6 hr; 17.3 | 10 hr; 9.0 | 24 hr; 1.6

Excretion of trimethoprim and sulfadiazine is chiefly by the kidneys, by both glomerular filtration and tubular secretion. Urine concentrations of both trimethoprim and sulfadiazine are several fold higher than blood concentrations. Neither trimethoprim nor sulfadiazine interferes with the excretion pattern of the other.

INDICATIONS AND USAGE

UNIPRIM POWDER FOR HORSES is indicated in horses where potent systemic antibacterial action against sensitive organisms is required. UNIPRIM POWDER FOR HORSES is indicated where control of bacterial infections is required during treatment of:

Acute Strangles | Acute Urogenital Infections
Respiratory Tract Infections | Wound Infections and Abscesses

UNIPRIM POWDER FOR HORSES is well tolerated by foals.

CONTRAINDICATIONS

Trimethoprim and sulfadiazine should not be used in horses showing marked liver parenchymal damage, blood dyscrasias, or in those with history of sulfonamide sensitivity.

WARNING

Do not use in horses intended for human consumption. Keep UNIPRIM POWDER FOR HORSES in a secure location out of reach of dogs, cats, and other animals to prevent accidental ingestion or overdose.

ADVERSE REACTIONS

During clinical trials, one case of anorexia and one case of loose feces following treatment with the drug were reported.

Individual animal hypersensitivity may result in local or generalized reactions, sometimes fatal. Anaphylactoid reactions, although rare, may also occur.

Antidote: Epinephrine.

To report suspected adverse drug events, for technical assistance or to obtain a copy of the Safety Data Sheet (SDS), contact Neogen Corporation at 859-254-1221 or neogen.com.

For additional information about adverse drug experience reporting for animal drugs, contact FDA at 1-888-FDA-VETS or online at www.fda.gov/reportanimalae.

Post Approval Experience: Horses have developed diarrhea during trimethoprim and sulfadiazine treatment, which could be fatal. If fecal consistency changes during trimethoprim and sulfadiazine therapy, discontinue treatment immediately and contact your veterinarian.

PRECAUTION

Water should be readily available to horses receiving sulfonamide therapy.

ANIMAL SAFETY

Toxicity is low. The acute toxicity (LD50) of trimethoprim and sulfadiazine is more than 5 g/kg orally in rats and mice. No significant changes were recorded in rats given doses of 600 mg/kg per day for 90 days.

Horses treated intravenously with trimethoprim and sulfadiazine 48% injection have tolerated up to five times the recommended daily dose for 7 days or on the recommended daily dose for 21 consecutive days without clinical effects or histopathological changes.

Lengthening of clotting time was seen in some of the horses on high or prolonged dosing in one of two trials. The effect, which may have been related to a resolving infection, was not seen in a second similar trial.

Slight to moderate reductions in hematopoietic activity following high, prolonged dosage in several species have been recorded. This is usually reversible by folinic acid (leucovorin) administration or by stopping the drug. During long-term treatment of horses, periodic platelet counts and white and red blood cell counts are advisable.

TERATOLOGY

The effect of trimethoprim and sulfadiazine on pregnancy has not been determined. Studies to date show there is no detrimental effect on stallion spermatogenesis with or following the recommended dose of trimethoprim and sulfadiazine.

DOSAGE AND ADMINISTRATION

The recommended dose is 3.75 g UNIPRIM POWDER FOR HORSES per 110 lbs (50 kg) body weight per day. Administer UNIPRIM POWDER FOR HORSES orally once a day in a small amount of palatable feed.

Dose Instructions: One 37.5 g packet is sufficient to treat 1100 lbs (500 kg) of body weight. For the 200 g, 400 g, and 1200 g jars, and 2000 g pail, two level, loose-filled, 32 cc scoops contain 37.5 g, sufficient to treat 1100 lbs (500 kg) of body weight. Since product contents may settle, gentle agitation during scooping is recommended.

The usual course of treatment is a single, daily dose for 5 to 7 days.

Continue acute infection therapy for 2 or 3 days after clinical signs have subsided.

If no improvement of acute infections is seen in 3 to 5 days, reevaluate the diagnosis.

UNIPRIM POWDER FOR HORSES may be used alone or in conjunction with intravenous dosing. Following treatment with trimethoprim and sulfadiazine 48% injection, therapy can be maintained using oral Powder.

A complete blood count should be done periodically in patients receiving UNIPRIM POWDER FOR HORSES for prolonged periods. If significant reduction in the count of any formed blood element is noted, treatment with UNIPRIM POWDER FOR HORSES should be discontinued.

STORAGE

Store at or below 25°C (77°F)

How Supplied

UNIPRIM POWDER FOR HORSES is available in 37.5 g packets, 200 g jars, 400 g jars, 2000 g pails. Apple Flavored UNIPRIM POWDER FOR HORSES is available in 37.5 g packets, 200 g jars, 400 g jars, 1200 g jars, and 2000 g pails.

CAUTION

Federal (USA) law restricts this drug to use by or on the order of a licensed veterinarian.

Approved by FDA under ANADA # 200-033

Manufactured by: Neogen Corporation

Lexington, KY 40511 USA • 859-254-1221

neogen.com

PRINCIPAL DISPLAY PANEL - 400 g Jar

NDC: 59051-3010-3

UNIPRIM®
POWDER FOR HORSES

(trimethoprim and sulfadiazine)

CAUTION: Federal (USA) law restricts this drug to use by or on the order of a licensed veterinarian.

NEOGENVet

Approved by FDA under ANADA # 200-033

Net Contents: 400 grams

FOR ANIMAL USE ONLY

Each gram contains:

Trimethoprim 67mg

Sulfadiazine 333mg

Indications:

For control of bacterial infections during treatment of acute strangles, respiratory tract infections, acute urogenital infections, wound infections, and abscesses.

Recommended Dose:

3.75 g per 110 lbs (50 kg) body weight once daily in a small amount of palatable feed. Two level, loose-filled, 32cc scoops contain 37.5g, sufficient to treat 1100 lbs (500 kg) body weight. Since product contents may settle, gentle agitation during scooping is recommended.

See package onsert for additional information.

KEEP OUT OF REACH OF CHILDREN

Store at or below 25°C (77°F)

Warning:

Do not use in horses intended for human consumption. Keep UNIPRIM POWDER FOR HORSES in a secure location out of reach of dogs, cats, and other animals to prevent accidental ingestion or overdose.

Manufactured by: Neogen Corporation

Lexington, KY 40511 USA • 859-254-1221

neogen.com L3438-0420

Item No. UP400

Rev. 05/23

Made in USA of U.S. and imported materials

PRINCIPAL DISPLAY PANEL - 200 g Jar

NDC: 59051-3010-4

UNIPRIM®
POWDER FOR HORSES

(trimethoprim and sulfadiazine)

CAUTION: Federal (USA) law restricts this drug to use by or on the order of a licensed veterinarian.

NEOGENVet

Approved by FDA under ANADA # 200-033

Net Contents: 200 grams

FOR ANIMAL USE ONLY

Each gram contains:

Trimethoprim 67mg

Sulfadiazine 333mg

Indications:

For control of bacterial infections during treatment of acute strangles, respiratory tract infections, acute urogenital infections, wound infections, and abscesses.

Recommended Dose:

3.75 g per 110 lbs (50 kg) body weight once daily in a small amount of palatable feed. Two level, loose-filled, 32cc scoops contain 37.5g, sufficient to treat 1100 lbs (500 kg) body weight. Since product contents may settle, gentle agitation during scooping is recommended.

See package onsert for additional information.

KEEP OUT OF REACH OF CHILDREN

Store at or below 25°C (77°F)

Warning:

Do not use in horses intended for human consumption. Keep UNIPRIM POWDER FOR HORSES in a secure location out of reach of dogs, cats, and other animals to prevent accidental ingestion or overdose.

Manufactured by: Neogen Corporation
Lexington, KY 40511 USA • 859-254-1221

neogen.com L3435-0420

Item No. UP200

Rev. 05/23

Made in USA of U.S. and imported materials

PRINCIPAL DISPLAY PANEL - 37.5 g Pouch

NDC: 59051-3010-1

UNIPRIM®
POWDER FOR HORSES

(trimethoprim and sulfadiazine)

CAUTION: Federal (USA) law restricts this drug to use by or on the order of a licensed veterinarian.

NEOGENVet

Approved by FDA under ANADA # 200-033

Net Contents: 37.5 grams

FOR ANIMAL USE ONLY

Each gram contains:

Trimethoprim 67mg

Sulfadiazine 333mg

Indications:

For control of bacterial infections during treatment of acute strangles, respiratory tract infections, acute urogenital infections, wound infections, and abscesses.

Recommended Dose:

3.75 g per 110 lbs (50 kg) body weight once daily in a small amount of palatable feed.

One packet contains 37.5g, sufficient to treat 1100 lbs (500 kg) body weight.

See package insert for additional information.

Rev. 05/23

Made in USA of U.S. and imported materials

KEEP OUT OF REACH OF CHILDREN

Store at or below 25°C (77°F)

Warning:

Do not use in horses intended for human consumption. Keep UNIPRIM POWDER FOR HORSES in a secure location out of reach of dogs, cats, and other animals to prevent accidental ingestion or overdose.

Manufactured by: Neogen Corporation
Lexington, KY 40511 USA • 859-254-1221

neogen.com L3413-0420

Item No. UP375

PRINCIPAL DISPLAY PANEL - 2000 g Pail

NDC: 59051-3010-6

UNIPRIM®
POWDER FOR HORSES

(trimethoprim and sulfadiazine)

CAUTION: Federal (USA) law restricts this drug to use by or on the order of a licensed veterinarian.

NEOGENVet

Approved by FDA under ANADA # 200-033

Net Contents: 2000 grams

FOR ANIMAL USE ONLY

Each gram contains:

Trimethoprim 67mg

Sulfadiazine 333mg

Indications:

For control of bacterial infections during treatment of acute strangles, respiratory tract infections, acute urogenital infections, wound infections, and abscesses.

Recommended Dose:

3.75 g per 110 lbs (50 kg) body weight once daily in a small amount of palatable feed. Two level, loose-filled, 32cc scoops contain 37.5g, sufficient to treat 1100 lbs (500 kg) body weight. Since product contents may settle, gentle agitation during scooping is recommended.

See package onsert for additional information.

KEEP OUT OF REACH OF CHILDREN

Store at or below 25°C (77°F)

Warning:

Do not use in horses intended for human consumption. Keep UNIPRIM POWDER FOR HORSES in a secure location out of reach of dogs, cats, and other animals to prevent accidental ingestion or overdose.

Manufactured by: Neogen Corporation
Lexington, KY 40511 USA • 859-254-1221

neogen.com L3436-0420

Item No. UP2000

Rev. 05/23

Made in USA of U.S. and imported materials